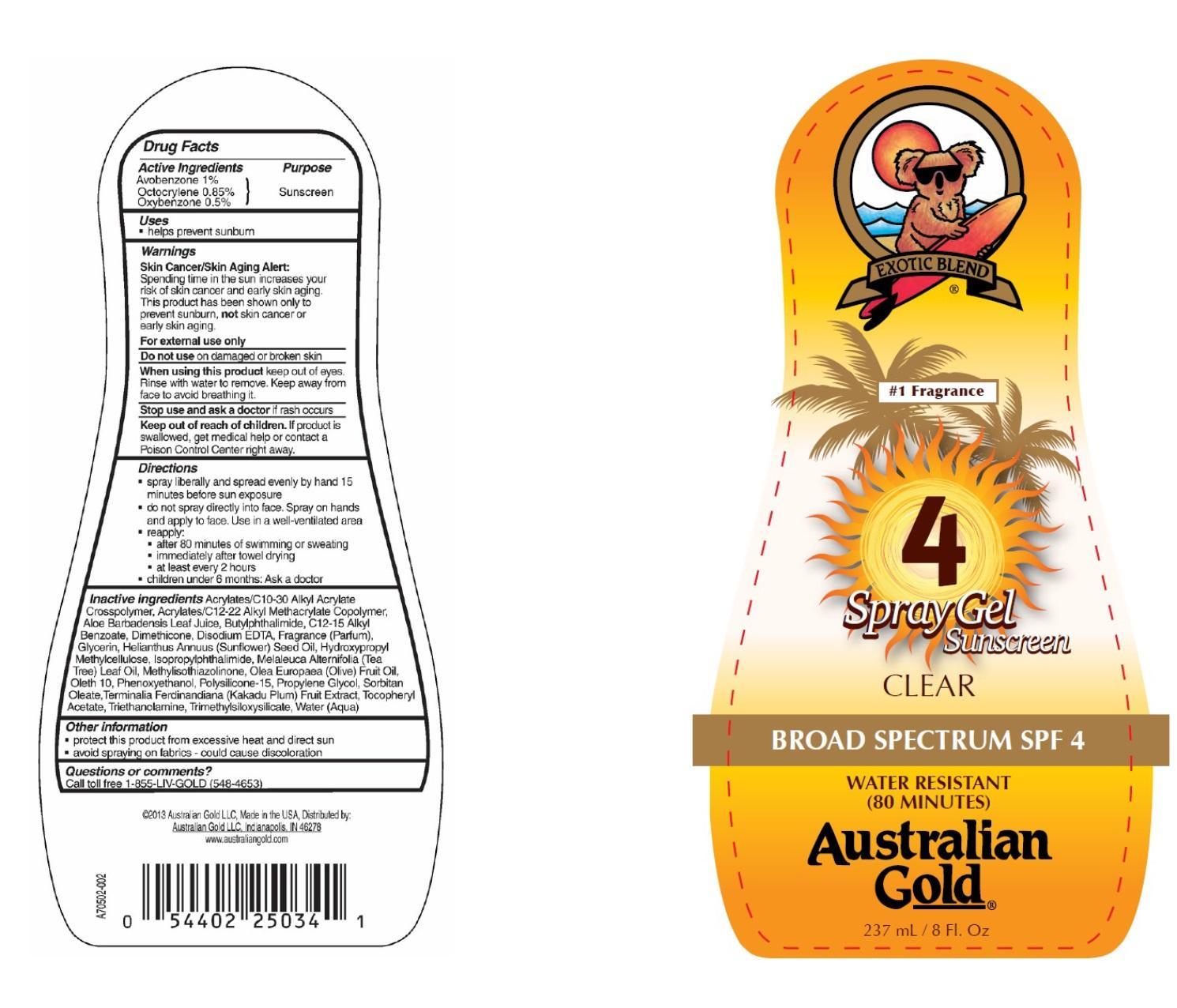 DRUG LABEL: Australian Gold
NDC: 58443-0076 | Form: GEL
Manufacturer: Prime Enterprises, Inc.
Category: otc | Type: HUMAN OTC DRUG LABEL
Date: 20200117

ACTIVE INGREDIENTS: AVOBENZONE 9.8 mg/1 mL; OCTOCRYLENE 8.3 mg/1 mL; OXYBENZONE 4.9 mg/1 mL
INACTIVE INGREDIENTS: CARBOMER COPOLYMER TYPE B (ALLYL PENTAERYTHRITOL CROSSLINKED); BUTYL ACRYLATE/C16-C20 ALKYL METHACRYLATE/METHACRYLIC ACID/METHYL METHACRYLATE COPOLYMER; ALOE VERA LEAF; 3-BUTYLPHTHALIDE; ISOPROPYLPHTHALIMIDE; ALKYL (C12-15) BENZOATE; DIMETHICONE; TRIMETHYLSILOXYSILICATE (M/Q 0.6-0.8); EDETATE DISODIUM; SUNFLOWER OIL; HYPROMELLOSES; TEA TREE OIL; METHYLISOTHIAZOLINONE; OLIVE OIL; OLETH-10; PHENOXYETHANOL; POLYSILICONE-15; PROPYLENE GLYCOL; SORBITAN MONOOLEATE; .ALPHA.-TOCOPHEROL ACETATE; TROLAMINE; KAKADU PLUM; WATER; GLYCERIN

Active ingredients

Avobenzone 1 %, Octocrylene 0.85 %, and Oxybenzone 0.5 %

Purpose

Sunscreen

Uses

- helps prevent sunburn

Warnings

Skin Cancer/Skin Aing Alert:

Spending time in the sun increases your risk of skin cancer and early skin aging. This product has been shown only to prevent sunburn, not skin cancer or early skin aging.

OTHER SAFETY INFORMATION

For external use only

Do not use on damaged or broken skin.

When using this product keep out of eyes. Rinse with water to remove. Keep away from face to avoid breathing it.

Stop use and ask a doctor if rash occurs.

Keep out of reach of children. If product is swallowed, get medical help or contact a Poison Control Center right away.

Directions

- spray liberally and spread evenly by hand 15 minutes before sun exposure
- hold container 4 to 6 inches from the skin to apply
- do not spray directly into face. Spray on hands and apply to face. Use in a well-ventilated area
- reapply
  - after 80 minutes of swimming or sweating
  - immediately after towel drying
  - at least every 2 hours
- children under 6 months: Ask a doctor

Inactive Ingredients

Acrylates/C10-30 Alkyl Acrylate Crosspolymer, Acrylates/C12-22 Alkyl Methacrylate Copolymer, Aloe Barbadensis Leaf Juice, Butylphthalimide, C12-15 Alkyl Benzoate, Dimethicone, Disodium EDTA, Fragrance (Parfum), Glycerin, Helianthus Annuus (Sunflower) Seed Oil, Hydroxypropyl Methylcellulose, Isopropylphthalimide, Melaleuca Alternifolia (Tea Tree) Leaf Oil, Methylisothiazolinone, Olea Europaea (Olive) Fruit Oil, Oleth 10, Phenoxyethanol, Polysilicone-15, Propylene Glycol, Sorbitan Oleate,Terminalia Ferdinandiana (Kakadu Plum) Fruit Extract, Tocopheryl Acetate, Triethanolamine, Trimethylsiloxysilicate, Water (Aqua)

Other information

- protect this product from excesive heat and direct sun
- avoid spraying on fabics - could cause discoloration

Questions or Comments?

Call toll free 1-855-LIV-GOLD (548-4653)

PRINCIPAL DISPLAY PANEL - 237 mL Bottle Label

EXOTIC BLEND

#1 Fragrance

4

Spray Gel Sunscreen

CLEAR

BROAD SPECTRUM SPF 4

WATER RESISTANT

(80 MINUTES)

Australian

Gold

237 mL / 8 Fl. Oz